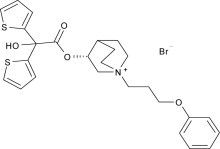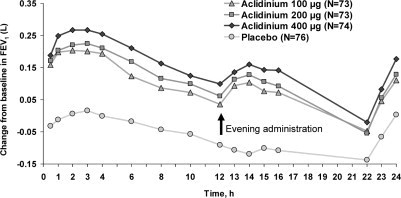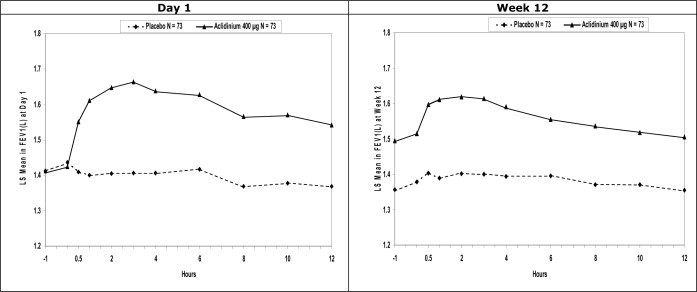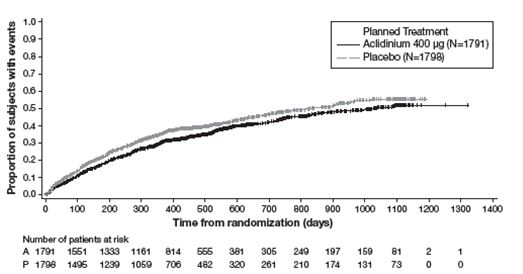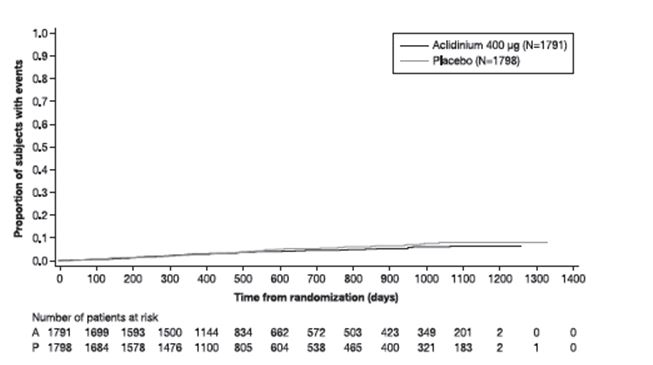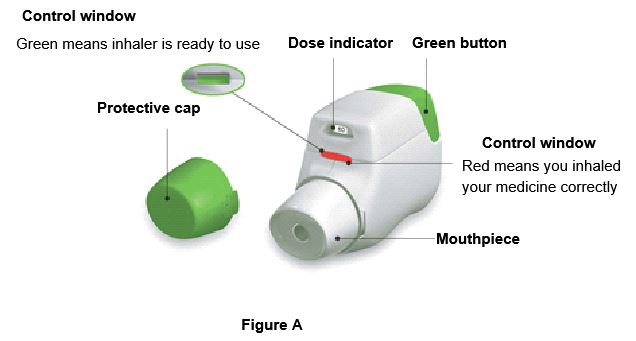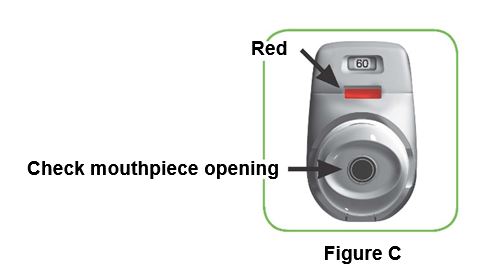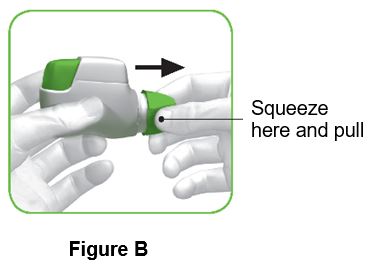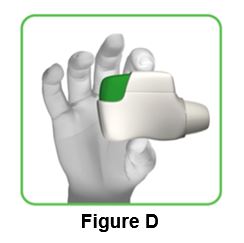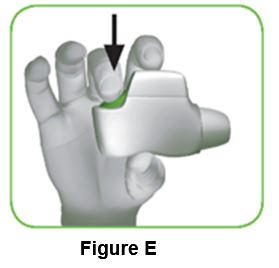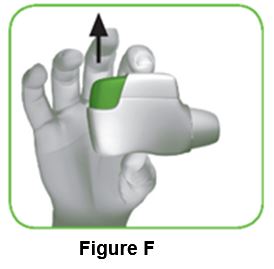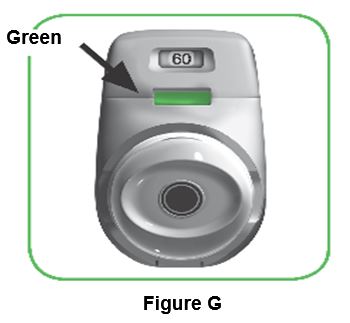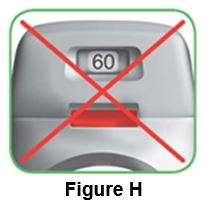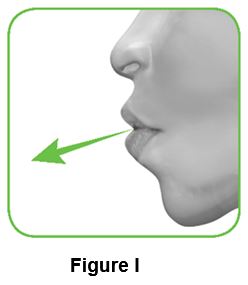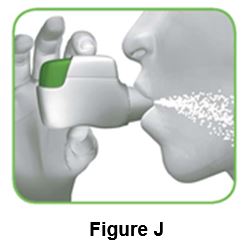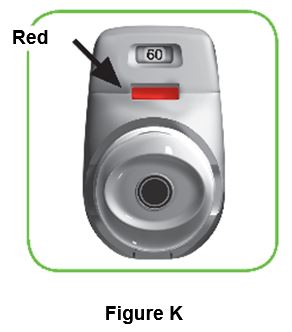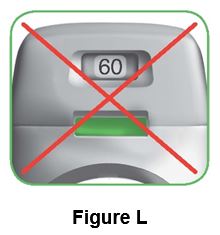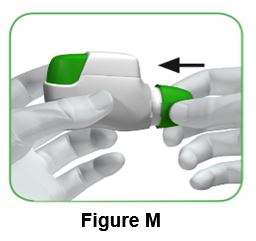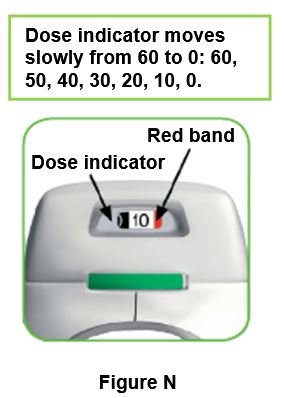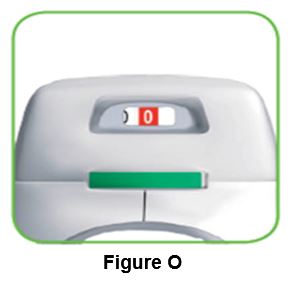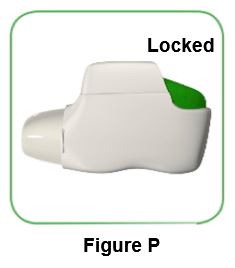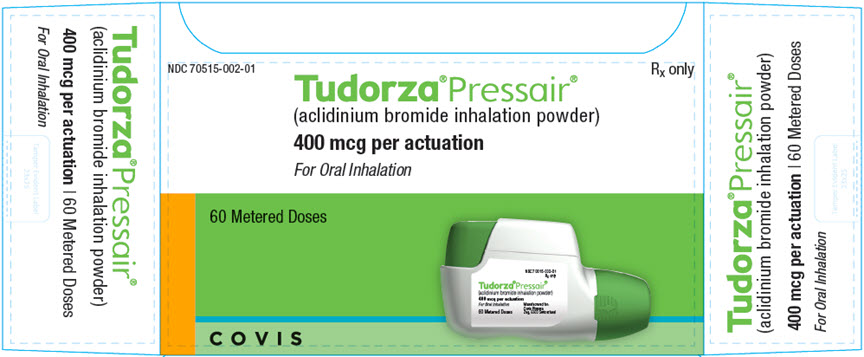 DRUG LABEL: Tudorza Pressair
NDC: 70515-002 | Form: POWDER, METERED
Manufacturer: Covis Pharma US, Inc
Category: prescription | Type: HUMAN PRESCRIPTION DRUG LABEL
Date: 20220801

ACTIVE INGREDIENTS: ACLIDINIUM BROMIDE 400 ug/1 1
INACTIVE INGREDIENTS: lactose monohydrate

HIGHLIGHTS OF PRESCRIBING INFORMATION

These highlights do not include all the information needed to use TUDORZA PRESSAIR safely and effectively. See full prescribing information for TUDORZA PRESSAIR.
TUDORZA® PRESSAIR® (aclidinium bromide inhalation powder)
FOR ORAL INHALATION ONLY
Initial U.S. Approval: 2012

1 INDICATIONS AND USAGE

TUDORZA PRESSAIR is an anticholinergic indicated for the maintenance treatment of patients with chronic obstructive pulmonary disease (COPD). (1)

2 DOSAGE AND ADMINISTRATION

For oral inhalation only

- One inhalation of TUDORZA PRESSAIR 400 mcg twice daily. (2)

3 DOSAGE FORMS AND STRENGTHS

- Inhalation powder; The multi-dose device is a dry powder inhaler metering 400 mcg of aclidinium bromide per actuation. (3)

4 CONTRAINDICATIONS

- Severe hypersensitivity to milk proteins. (4)
- Hypersensitivity to any ingredient. (4)

5 WARNINGS AND PRECAUTIONS

- Not for acute use: Not for use as a rescue medication. (5.1)
- Paradoxical bronchospasm: Discontinue TUDORZA PRESSAIR and consider other treatments if paradoxical bronchospasm occurs. (5.2)
- Worsening of narrow-angle glaucoma may occur. Use with caution in patients with narrow-angle glaucoma and instruct patients to consult a physician immediately if this occurs. (5.3)
- Worsening of urinary retention may occur. Use with caution in patients with prostatic hyperplasia or bladder-neck obstruction and instruct patients to consult a physician immediately if this occurs. (5.4)
- Immediate hypersensitivity reactions: Discontinue TUDORZA PRESSAIR at once and consider alternatives if immediate hypersensitivity reactions, including angioedema, bronchospasm, or anaphylaxis occur. (5.5)

6 ADVERSE REACTIONS

Most common adverse reactions (≥3% incidence and greater than placebo) are headache, nasopharyngitis and cough. (6.1)

To report SUSPECTED ADVERSE REACTIONS, contact Covis Pharma at 1-877-411-2510 or FDA at 1-800-FDA-1088 or www.fda.gov/medwatch.

7 DRUG INTERACTIONS

Anticholinergics: May interact additively with concomitantly used anticholinergic medications. Avoid administrations of TUDORZA PRESSAIR with other anticholinergic-containing drugs. (7.2)

FULL PRESCRIBING INFORMATION

1 INDICATIONS AND USAGE

TUDORZA® PRESSAIR® (aclidinium bromide inhalation powder) is indicated for the maintenance treatment of patients with chronic obstructive pulmonary disease (COPD).

2 DOSAGE AND ADMINISTRATION

The recommended dose of TUDORZA PRESSAIR is one oral inhalation of 400 mcg, twice daily (morning and evening approximately 12 hours apart).

3 DOSAGE FORMS AND STRENGTHS

Inhalation Powder. TUDORZA PRESSAIR is a breath-actuated multi-dose dry powder inhaler metering 400 mcg of aclidinium bromide per actuation.

4 CONTRAINDICATIONS

The use of TUDORZA PRESSAIR is contraindicated in the following conditions:

- Severe hypersensitivity to milk proteins [see Warnings and Precautions (5.5)]
- Hypersensitivity to aclidinium bromide or any of the excipients [see Warnings and Precautions (5.5)]

5 WARNINGS AND PRECAUTIONS

5.1 Not for Acute Use

TUDORZA PRESSAIR is intended as a twice-daily maintenance treatment for COPD and is not indicated for the initial treatment of acute episodes of bronchospasm (i.e., rescue therapy).

5.2 Paradoxical Bronchospasm

Inhaled medicines, including TUDORZA PRESSAIR, may cause paradoxical bronchospasm. If this occurs, treatment with TUDORZA PRESSAIR should be stopped and other treatments considered.

5.3 Worsening of Narrow-Angle Glaucoma

TUDORZA PRESSAIR should be used with caution in patients with narrow-angle glaucoma. Prescribers and patients should be alert for signs and symptoms of acute narrow-angle glaucoma (e.g., eye pain or discomfort, blurred vision, visual halos, or colored images in association with red eyes from conjunctival congestion and corneal edema). Instruct patients to consult a physician immediately should any of these signs or symptoms develop.

5.4 Worsening of Urinary Retention

TUDORZA PRESSAIR should be used with caution in patients with urinary retention. Prescribers and patients should be alert for signs and symptoms of prostatic hyperplasia or bladder-neck obstruction (e.g., difficulty passing urine, painful urination). Instruct patients to consult a physician immediately should any of these signs or symptoms develop.

5.5 Immediate Hypersensitivity Reactions

Immediate hypersensitivity reactions, including anaphylaxis, angioedema (including swelling of the lips, tongue, or throat), urticaria, rash, bronchospasm, or itching, have occurred after administration of TUDORZA PRESSAIR. If such a reaction occurs, therapy with TUDORZA PRESSAIR should be stopped at once and alternative treatments should be considered.

6 ADVERSE REACTIONS

The following adverse reactions are described in greater detail in other sections:

- Paradoxical bronchospasm [see Warnings and Precautions (5.2)]
- Worsening of narrow-angle glaucoma [see Warnings and Precautions (5.3)]
- Worsening of urinary retention [see Warnings and Precautions (5.4)]
- Immediate hypersensitivity reactions [see Warnings and Precautions (5.5)]

6.1 Clinical Trials Experience

Because clinical trials are conducted under widely varying conditions, adverse reaction rates observed in the clinical trials of a drug cannot be directly compared to rates in the clinical trials of another drug and may not reflect the rates observed in practice.

3-Month and 6-Month Trials

TUDORZA PRESSAIR was studied in two 3-month (Trials B and C) and one 6-month (Trial D) placebo-controlled trials in patients with COPD. In these trials, 636 patients were treated with TUDORZA PRESSAIR at the recommended dose of 400 mcg twice daily.

The population had a mean age of 64 years (ranging from 40 to 89 years), with 58% males, 94% Caucasian, and had COPD with a mean pre-bronchodilator forced expiratory volume in one second (FEV1) percent predicted of 48%. Patients with unstable cardiac disease, narrow-angle glaucoma, or symptomatic prostatic hypertrophy or bladder outlet obstruction were excluded from these trials.

Table 1 shows all adverse reactions that occurred with a frequency of greater than or equal to 1% in the TUDORZA PRESSAIR group in the two 3-month and one 6-month placebo-controlled trials where the rates in the TUDORZA PRESSAIR group exceeded placebo.

Table 1: Adverse Reactions (% Patients) in Placebo-Controlled Clinical Trials
 | Treatment
Adverse Reactions | TUDORZA PRESSAIR | Placebo
Preferred Term | (N=636) | (N=640)
 | n (%) | n (%)
Headache | 42 (6.6) | 32 (5.0)
Nasopharyngitis | 35 (5.5) | 25 (3.9)
Cough | 19 (3.0) | 14 (2.2)
Diarrhea | 17 (2.7) | 9 (1.4)
Sinusitis | 11 (1.7) | 5 (0.8)
Rhinitis | 10 (1.6) | 8 (1.2)
Toothache | 7 (1.1) | 5 (0.8)
Fall | 7 (1.1) | 3 (0.5)
Vomiting | 7 (1.1) | 3 (0.5)

In addition, among the adverse reactions observed in the clinical trials with an incidence of less than 1% were diabetes mellitus, dry mouth, 1st degree AV block, osteoarthritis, cardiac failure, and cardio-respiratory arrest.

Long-term Safety Trials

TUDORZA PRESSAIR was studied in three long-term safety trials, two double blind and one open label, ranging from 40 to 52 weeks in patients with moderate to severe COPD. Two of these trials were extensions of the 3-month trials, and one was a dedicated long-term safety trial. In these trials, 891 patients were treated with TUDORZA PRESSAIR at the recommended dose of 400 mcg twice daily. The demographic and baseline characteristics of the long-term safety trials were similar to those of the placebo-controlled trials. The adverse events reported in the long-term safety trials were similar to those occurring in the placebo-controlled trials of 3 to 6 months. No new safety findings were reported compared to the placebo-controlled trials.

Long-Term Trial of up to 3-Years

In a long-term safety trial with 3630 moderate to very severe COPD patients with previous major cardiac events or cardiovascular risk factors at baseline, the adverse reactions reported with a frequency ≥2% in the TUDORZA PRESSAIR group in which the exposure-adjusted incidence rate exceeds the placebo group were nausea, back pain, cough, hypertension, sinusitis, constipation, arthralgia, anemia, muscle spasms, cardiac failure congestive, cellulitis, and gastroesophageal reflux disease. No other new adverse reactions were identified.

6.2 Postmarketing Experience

The following adverse reactions have been identified during postapproval use of drug TUDORZA PRESSAIR. Because these reactions are reported voluntarily from a population of uncertain size, it is not always possible to reliably estimate their frequency or establish a causal relationship to drug exposure.

In postmarketing experience with TUDORZA PRESSAIR, immediate hypersensitivity reactions, including anaphylaxis, angioedema (including swelling of the lips, tongue, or throat), urticaria, rash, bronchospasm, or itching have been reported. Additionally, nausea, dysphonia, blurred vision, urinary retention, tachycardia, and stomatitis have been observed.

7 DRUG INTERACTIONS

In vitro studies suggest limited potential for CYP450-related metabolic drug interactions, thus no formal drug interaction studies have been performed with TUDORZA PRESSAIR [see Clinical Pharmacology (12.3)].

7.1 Sympathomimetics, Methylxanthines, Steroids

In clinical studies, concurrent administration of aclidinium bromide and other drugs commonly used in the treatment of COPD including sympathomimetics (short-acting beta2 agonists), methylxanthines, and oral and inhaled steroids showed no increases in adverse drug reactions.

7.2 Anticholinergics

There is a potential for an additive interaction with concomitantly used anticholinergic medications. Therefore, avoid coadministration of TUDORZA PRESSAIR with other anticholinergic-containing drugs as this may lead to an increase in anticholinergic effects.

8 USE IN SPECIFIC POPULATIONS

8.1 Pregnancy

Risk Summary

There are no adequate and well controlled studies of TUDORZA PRESSAIR in pregnant women to inform drug associated risks.

No adverse developmental effects were seen with inhalation administration of aclidinium bromide to pregnant rats and rabbits during organogenesis at 15 or 20 times, respectively, the maximum recommended human daily inhaled dose (MRHDID). However, reduced pup weights were seen when pregnant rats continued inhalation administration through lactation at 5 times the MRHDID of aclidinium bromide. Adverse developmental effects occurred when rabbits were orally dosed with aclidinium bromide at approximately 1,400 times the MRHDID [see Data].

The estimated background risk of major birth defects and miscarriage of the indicated populations is unknown. In the U.S. general population, the estimated background risk of major birth defects and miscarriage in clinically recognized pregnancies is 2% to 4% and 15% to 20%, respectively.

Data

Animal Data

In an embryo-fetal development study in pregnant rats dosed during the period of organogenesis from gestation days 6-17, no evidence of structural alterations was observed at approximately 15 times the MRHDID [based on summed AUCs of aclidinium bromide and its metabolites at inhaled doses less than or equal to 5.0 mg/kg/day]. However, in a pre- and post-natal development study, decreased pup weights were observed when pregnant rats were exposed from gestation day 6 and continuing during the lactation period at approximately 5 times the MRHDID [based on summed AUCs of aclidinium bromide and its metabolites at inhaled doses greater than or equal to 0.2 mg/kg/day]. Maternal toxicity was also observed at inhaled doses greater than or equal to 0.2 mg/kg/day.

In an embryo-fetal development study in pregnant Himalayan rabbits administered inhaled doses of aclidinium bromide during the period of organogenesis from gestation days 6-19, no evidence of structural alterations was observed at approximately 20 times the MRHDID [based on summed AUCs of aclidinium bromide and its metabolites at inhaled doses less than or equal to 3.6 mg/kg/day]. However, in another embryo-fetal development study in pregnant Himalayan rabbits dosed orally from gestation days 6-19, increased incidences of additional liver lobes (3-5%), as compared to 0% in the control group, were observed at approximately 1,400 times the MRHDID [based on summed AUCs of aclidinium bromide and its metabolites at oral doses greater than or equal to 150 mg/kg/day], and decreased fetal body weights were observed at approximately 2,300 times the MRHDID [based on summed AUCs of aclidinium bromide and its metabolites at oral doses greater than or equal to 300 mg/kg/day]. These fetal findings were observed in the presence of maternal toxicity.

8.2 Lactation

Risk Summary

There are no available data on the effects of TUDORZA PRESSAIR or aclidinium bromide on the breastfed child or on milk production or presence in human milk. Aclidinium bromide is present in milk of lactating female rats [see Data]. When a drug is present in animal milk, it is likely that the drug will be present in human milk. The developmental and health benefits of breastfeeding should be considered along with the mother’s clinical need for TUDORZA PRESSAIR and any potential adverse effects on the breastfed child from TUDORZA PRESSAIR or from the underlying maternal condition.

Data

In a pharmacokinetic study, levels of radioactivity in milk and plasma in rats were measured after a single intravenous dose of 1 mg/kg of radiolabeled aclidinium bromide on approximately post-natal day 14 [see Use in Specific Populations (8.1)]. The maximum concentration of radioactivity [^14C-aclidinium] in milk was measured at 6 hours post-dose and was found to be 10-14 times higher than in plasma.

8.4 Pediatric Use

TUDORZA PRESSAIR is approved for use in the maintenance treatment of bronchospasm associated with COPD. COPD does not normally occur in children. The safety and effectiveness of TUDORZA PRESSAIR in pediatric patients have not been established.

8.5 Geriatric Use

Of the 636 COPD patients exposed to TUDORZA PRESSAIR 400 mcg twice daily for up to 24 weeks in three placebo-controlled clinical trials, 197 were less than 60 years, 272 were greater than or equal to 60 to less than 70 years, and 167 were greater than or equal to 70 years of age. No overall differences in safety or effectiveness were observed between these subjects and younger subjects. Other reported clinical experience has not identified differences in responses between the elderly and younger patients, but greater sensitivity of some older individuals cannot be ruled out. Based on available data for TUDORZA PRESSAIR, no adjustment of dosage in geriatric patients is warranted [see Clinical Pharmacology (12.3)].

8.6 Renal Impairment

The pharmacokinetics of TUDORZA PRESSAIR were investigated in subjects with normal renal function and in subjects with mild, moderate, and severe renal impairment [see Clinical Pharmacology (12.3)]. No clinically significant differences in aclidinium pharmacokinetics were noted between these populations. Based on available data for TUDORZA PRESSAIR, no adjustment of dosage in renally impaired subjects is warranted.

8.7 Hepatic Impairment

The effects of hepatic impairment on the pharmacokinetics of TUDORZA PRESSAIR were not studied [see Clinical Pharmacology (12.3)].

10 OVERDOSAGE

10.1 Human Experience

No case of overdose has been reported in clinical studies with TUDORZA PRESSAIR. There were no systemic anticholinergic or other adverse effects following a single inhaled dose of up to 6,000 mcg aclidinium bromide (7.5 times the RHDD) in 16 healthy volunteers.

11 DESCRIPTION

TUDORZA PRESSAIR consists of a dry powder formulation of aclidinium bromide for oral inhalation only.

Aclidinium bromide, the active component of TUDORZA PRESSAIR is an anticholinergic with specificity for muscarinic receptors. Aclidinium bromide is a synthetic, quaternary ammonium compound, chemically described as 1-azoniabicyclo[2.2.2]octane, 3-[(hydroxydi-2-thienylacetyl)oxy]-1-(3-phenoxypropyl)-, bromide, (3R)-. The structural formula is:

Aclidinium bromide is a white powder with a molecular formula of C26H30NO4S2Br and a molecular mass of 564.56. It is very slightly soluble in water and ethanol and sparingly soluble in methanol.

TUDORZA PRESSAIR is a breath-actuated multi-dose dry powder inhaler. Each actuation of TUDORZA PRESSAIR provides a metered dose of 13 mg of the formulation which contains lactose monohydrate (which may contain milk proteins) as the carrier and 400 mcg of aclidinium bromide (equivalent to 343 mcg of aclidinium). This results in delivery of 375 mcg aclidinium bromide (equivalent to 322 mcg of aclidinium) from the mouthpiece, based on in vitro testing at an average flow rate of 63 L/min with constant volume of 2 L. The amount of drug delivered to the lungs will vary depending on patient factors such as inspiratory flow rate and inspiratory time.

12 CLINICAL PHARMACOLOGY

12.1 Mechanism of Action

Aclidinium bromide is a long-acting antimuscarinic agent, which is often referred to as an anticholinergic. It has similar affinity to the subtypes of muscarinic receptors M1 to M5. In the airways, it exhibits pharmacological effects through inhibition of M3 receptor at the smooth muscle leading to bronchodilation. The competitive and reversible nature of antagonism was shown with human and animal origin receptors and isolated organ preparations. In preclinical in vitro as well as in vivo studies, prevention of acetylcholine-induced bronchoconstriction effects was dose-dependent and lasted longer than 24 hours. The clinical relevance of these findings is unknown. The bronchodilation following inhalation of aclidinium bromide is predominantly a site-specific effect.

12.2 Pharmacodynamics

Cardiovascular Effects

In a thorough QT Study, 200 mcg and 800 mcg TUDORZA PRESSAIR was administered to healthy volunteers once daily for 3 days; no effects on prolongation of QT interval were observed using QTcF heart-rate correction methods.

Additionally, the effect of TUDORZA PRESSAIR on cardiac rhythm was assessed in 336 COPD patients, 164 patients received aclidinium bromide 400 mcg twice daily and 172 patients received placebo, using 24-hr Holter monitoring. No clinically significant effects on cardiac rhythm were observed.

12.3 Pharmacokinetics

Absorption

The absolute bioavailability of aclidinium bromide is approximately 6% in healthy volunteers. Following twice-daily oral inhalation administration of 400 mcg aclidinium bromide in healthy subjects, peak steady state plasma levels were observed within 10 minutes after inhalation.

Distribution

Aclidinium bromide shows a volume of distribution of approximately 300 L following intravenous administration of 400 mcg in humans.

Metabolism

Clinical pharmacokinetics studies, including a mass balance study, indicate that the major route of metabolism of aclidinium bromide is hydrolysis, which occurs both chemically and enzymatically by esterases. Aclidinium bromide is rapidly and extensively hydrolyzed to its alcohol and dithienylglycolic acid derivatives, neither of which binds to muscarinic receptors and are devoid of pharmacologic activity.

Therefore, due to the low plasma levels achieved at the clinically relevant doses, aclidinium bromide and its metabolites are not expected to alter the disposition of drugs metabolized by the human CYP450 enzymes.

Elimination

Total clearance was approximately 170 L/h after an intravenous dose of aclidinium bromide in young healthy volunteers with an inter-individual variability of 36%. Intravenously administered radiolabeled aclidinium bromide was administered to healthy volunteers and was extensively metabolized with 1% excreted as unchanged aclidinium. Approximately 54% to 65% of the radioactivity was excreted in urine and 20% to 33% of the dose was excreted in feces. The combined results indicated that almost the entire aclidinium bromide dose was eliminated by hydrolysis. After dry powder inhalation, urinary excretion of aclidinium is about 0.09% of the dose and the estimated effective half-life is 5 to 8 hours.

Drug Interactions

Formal drug interaction studies were not performed. In vitro studies using human liver microsomes indicated that aclidinium bromide and its major metabolites do not inhibit CYP450, 1A2, 2A6, 2B6, 2C8, 2C9, 2C19, 2D6, 2E1, 3A4/5, or 4A9/11 at concentrations up to 1,000-fold higher than the maximum plasma concentration that would be expected to be achieved at the therapeutic dose. Therefore, it is unlikely that aclidinium bromide causes CYP450 related drug interactions [see Drug Interactions (7)].

Specific Populations

Elderly Patients

The pharmacokinetic profile of aclidinium bromide and its main metabolites was assessed in 12 elderly COPD patients (aged 70 years or older) compared to a younger cohort of 12 COPD patients (40-59 years) that were administered 400 mcg aclidinium bromide once daily for 3 days via inhalation. No clinically significant differences in systemic exposure (AUC and Cmax) were observed when the two groups were compared. No dosage adjustment is necessary in elderly patients [see Use in Specific Populations (8.5)].

Renal Impairment

The impact of renal disease upon the pharmacokinetics of aclidinium bromide was studied in 18 subjects with mild, moderate, or severe renal impairment. Systemic exposure (AUC and Cmax) to aclidinium bromide and its main metabolites following single doses of 400 mcg aclidinium bromide was similar in renally impaired patients compared with 6 matched healthy control subjects. No dose adjustment is necessary in renally impaired patients [see Use in Specific Populations (8.6)].

Hepatic Impairment

The effects of hepatic impairment on the pharmacokinetics of aclidinium bromide were not studied. However, hepatic insufficiency is not expected to have relevant influence on aclidinium bromide pharmacokinetics, since it is predominantly metabolized by chemical and enzymatic hydrolysis to products that do not bind to muscarinic receptors [see Use in Specific Populations (8.7)].

13 NONCLINICAL TOXICOLOGY

13.1 Carcinogenesis, Mutagenesis, Impairment of Fertility

Two-year inhalation studies were conducted in mice and rats to assess the carcinogenic potential of aclidinium bromide. No evidence of tumorigenicity was observed in rats and mice at aclidinium doses up to 0.20 and 2.4 mg/kg/day, respectively [approximately 10 and 80 times the Maximum Recommended Human Daily Inhalation Dose (MRHDID), respectively, based on summed AUCs of aclidinium bromide and its metabolites].

Aclidinium bromide was positive in the in vitro bacterial gene mutation assay and the in vitro thymidine locus mouse lymphoma assay. However, aclidinium bromide was negative in the in vivo mouse micronucleus assay and the in vivo/in vitro unscheduled DNA synthesis assay with rat liver.

Aclidinium bromide impaired several fertility and reproductive performance indices (increased number of days to mate, decreased conception rate, decreased number of corpora lutea, increased pre-implantation loss with consequent decreased number of implantations, and live embryos) in both male and female rats administered inhaled doses greater than or equal to 0.8 mg/kg/day [approximately 15 times the MRHDID based on summed AUCs of aclidinium bromide and its metabolites]. These adverse fertility effects were observed in the presence of paternal toxicity as evidenced by mortality and decreased body weight gain. However, there were no effects on mating index and sperm number and morphology. In the separate fertility assessments (treated males mated with untreated females; treated females mated with untreated males), no effect was observed in male and female rats at inhaled doses of 1.9 and 0.8 mg/kg/day, respectively [approximately 30 and 15 times the MRHDID, respectively, based on summed AUCs of aclidinium bromide and its metabolites].

14 CLINICAL STUDIES

14.1 Chronic Obstructive Pulmonary Disease (COPD)

The TUDORZA PRESSAIR clinical development program included a dose-ranging trial (Trial A) for nominal dose selection and three confirmatory lung function trials (Trials B, C, and D). Two additional lung function trials (Trials E and F) of aclidinium bromide alone and as part of a fixed-dose combination product also provided information on the effect of TUDORZA PRESSAIR on the St. George’s Respiratory Questionnaire (SGRQ) total score compared to placebo. A long-term study of up to 3 years (Trial G) evaluated the effect of TUDORZA PRESSAIR on major adverse cardiovascular events and on COPD exacerbations.

Dose-ranging trial

Trial A (NCT01120093) was a randomized, double-blind, placebo-controlled, active-controlled, crossover trial with 7-day treatment periods separated by 5-day washout periods. Trial A enrolled 79 patients who had a clinical diagnosis of COPD were 40 years of age or older, had a history of smoking at least 10 pack-years, had a forced expiratory volume in one second (FEV1) of at least 30% and less than 80% of predicted normal value, and a ratio of FEV1 over forced vital capacity (FEV1/FVC) of less than 0.7. Trial A included TUDORZA PRESSAIR doses of 400 mcg, 200 mcg, and 100 mcg twice daily, formoterol active control, and placebo. Trial A demonstrated that the effect on trough FEV1 and serial FEV1 in patients treated with the TUDORZA PRESSAIR 100 mcg twice daily and 200 mcg twice daily doses was lower compared to patients treated with the TUDORZA PRESSAIR 400 mcg twice daily dose (Figure 1).

Figure 1: Change from baseline in FEV1 Over Time (prior to and after administration of study drug) at Week 1 in Trial A

Confirmatory trials

Trials B (NCT00891462), C (NCT01045161), and D (NCT01001494) were three randomized, double-blind, placebo-controlled trials in patients with COPD. Trials B and C were 3 months in duration, and Trial D was 6 months in duration. These trials enrolled 1,276 patients who had a clinical diagnosis of COPD, including chronic bronchitis and emphysema, were 40 years of age or older, had a history of smoking at least 10 pack-years, had an FEV1 of at least 30% and less than 80% of predicted normal value, and a ratio of FEV1/FVC of less than 0.7; 59% were male, and 93% were Caucasian.

These clinical trials evaluated TUDORZA PRESSAIR 400 mcg twice daily (636 patients) and placebo (640 patients). TUDORZA PRESSAIR 400 mcg resulted in statistically significantly greater bronchodilation as measured by change from baseline in morning pre-dose FEV1 at 12 weeks (the primary efficacy endpoint) compared to placebo in all three trials (Table 2).

Table 2: Change from Baseline in Trough FEV1 (L) at Week 12
Treatment Arm | Baseline | Change from Baseline LS Mean (SE) | Treatment Difference LS Mean (95% CI)
Trial B (N=375)
Aclidinium 400 mcg | 1.33 | 0.10 (0.01) | 0.12 (0.08, 0.16)
Placebo | 1.38 | -0.02 (0.02)
Trial C (N=359)
Aclidinium 400 mcg | 1.25 | 0.06 (0.02) | 0.07 (0.03, 0.12)
Placebo | 1.46 | -0.01 (0.02)
Trial D [In the 6-month Trial D, placebo adjusted change from baseline in Trough FEV1 at 24 weeks was 0.13 (0.09, 0.17).] (N=542)
Aclidinium 400 mcg | 1.51 | 0.06 (0.02) | 0.11 (0.07, 0.14)
Placebo | 1.50 | -0.05 (0.02)
SE=standard error, and LS mean=least square mean. LS mean, and 95% confidence interval were obtained from an ANCOVA model with change from baseline in trough FEV1 as response, with treatment group and sex as factors and baseline trough FEV1 and age as covariates.

Serial spirometric evaluations were performed throughout daytime hours in a subset of patients in the three trials. The serial FEV1 values over 12 hours for one of the 3-month trials (Trial B) are displayed in Figure 2. Results for the other two placebo-controlled trials were similar to the results for Trial B. Improvement of lung function was maintained for 12 hours after a single dose and was consistent over the 3- or 6-month treatment period.

Figure 2: Mean FEV1 Over Time (prior to and after administration of study drug) on Day 1 and Week 12 in Subset of Patients Participating in the 12 hours Serial Spirometry Substudy for Trial B (a 3-month Placebo-Controlled Study)

Mean peak improvements in FEV1, for TUDORZA PRESSAIR relative to baseline were assessed in all patients in trials B, C, and D after the first dose on Day 1 and were similar at Week 12. In Trials B and D, but not in Trial C, patients treated with TUDORZA PRESSAIR used less daily rescue albuterol during the trial compared to patients treated with placebo.

Trials E (NCT01437397) and F (NCT01462942) were two randomized, double-blind, placebo-controlled trials of an aclidinium bromide-containing fixed- dose combination product and its components compared to placebo in patients with COPD, including chronic bronchitis and emphysema. Trials E and F were 6 months in duration. These trials enrolled 3421 patients who had a clinical diagnosis of COPD, were 40 years of age or older, had a history of smoking at least 10 pack-years, had an FEV1 of at least 30% and less than 80%, and a ratio of FEV1/FVC less than 0.7; 60.5% were male, 94.1% were Caucasian.

The St. George’s Respiratory Questionnaire (SGRQ) was assessed in Trials D, E, and F at 6 months. In Trial D, the SGRQ responder rate (defined as an improvement in score of 4 or more as threshold) was 54.3% in TUDORZA PRESSAIR compared to 39.5% in placebo, with odds ratio of 1.77 (95% CI 1.25, 2.52). In Trial E, the SGRQ responder rate in the TUDORZA PRESSAIR group was 54.5% compared to 38.7% in the placebo group, with odds ratio of 2.18 (95% CI 1.37, 3.48). In Trial F, the SGRQ responder rate in the TUDORZA PRESSAIR group was 53.5% compared to 53.2% in the placebo group, with odds ratio of 0.99 (95% CI 0.6, 1.64).

Long Term Safety and Efficacy Trial of up to 3-years

Trial G (NCT01966107) was a randomized, double-blind, placebo-controlled study of up to 36 months that evaluated the effect of TUDORZA PRESSAIR on major adverse cardiovascular events and COPD exacerbations in patients with moderate to very severe COPD with and without a history of COPD exacerbations.

The trial enrolled 3630 patients with COPD, including chronic bronchitis and emphysema, between 40 and 91 years of age, 58.7% were male and 90.7% were Caucasian, with a mean post-bronchodilator FEV1 of 47.9% of predicted value. All patients had a history of cardiovascular or cerebrovascular disease and/or significant cardiovascular risk factors. All patients had moderate to very severe COPD. 60.1% of patients had at least one prior moderate or severe COPD exacerbation within the past 12 months from the screening visit, and 39.9% had no history of a moderate or severe COPD exacerbation within the past 12 months.

Approximately 48% of enrolled patients had a prior history of at least 1 documented previous CV event; cerebrovascular disease (13.1%), coronary artery disease (35.4%), peripheral vascular disease or history of claudication (13.6%); 63.6% of them were on long-acting β2-adrenergic agonist (LABA or LABA/inhaled corticosteroid (ICS) maintenance therapy at study entry (LABA only 6.3%, LABA/ICS 57.3%)). The majority of patients had moderate (45.1%) or severe (40.2%) airflow obstruction.

The primary safety endpoint was the time to first occurrence of a major adverse cardiovascular event (MACE), defined as any of the following adjudicated events: cardiovascular death, non-fatal myocardial infarction (MI), or non-fatal ischemic stroke. The study was designed to exclude a pre-specified risk margin of 1.8 for the hazard ratio of MACE.

The results of Trial G, including each component event of the primary composite endpoint, are shown in Table 3. The proportion of patients with at least one MACE was 3.9% in the TUDORZA PRESSAIR group compared to 4.2% in the placebo group. The incidence rate of MACE was 2.4 per 100 patient-years on TUDORZA PRESSAIR vs. 2.8 per 100 patient-years on placebo. The estimated hazard ratio of MACE associated with TUDORZA PRESSAIR relative to placebo was 0.89 with a 95% confidence interval of (0.64, 1.23). The upper bound of this confidence interval, 1.23, excluded a risk margin larger than 1.8. TUDORZA PRESSAIR was non-inferior to placebo for risk of major adverse cardiovascular events.

Table 3: Primary Analysis of Adjudicated Major Adverse Cardiovascular Events (MACE)
 | TUDORZA PRESSAIR |  | Placebo |  | Hazard Ratio (95% CI)
 | N = 1791 | Total PY = 2828.9 | N = 1798 | Total PY = 2748.1
 | Subjects with Events (%) | Rate per 100 PY | Subjects with Events (%) | Rate per 100 PY
MACE | 69 (3.9%) | 2.4 | 76 (4.2%) | 2.8 | 0.89 (0.64, 1.23)
Component Events [A patient may have experienced more than one component; therefore, the sum of the components is larger than the number of patients who experienced the composite outcome]
CV Death | 26 (1.5%) |  | 19 (1.1%)
Non-fatal MI | 28 (1.6%) |  | 38 (2.1%)
Non-fatal Ischemic Stroke | 18 (1.0%) |  | 24 (1.3%)

The study was powered to rule out a hazard ratio of 1.8 in time to first MACE in TUDORZA PRESSAIR-treated patients relative to placebo.

MACE: major adverse cardiovascular event; CV: cardiovascular; MI: myocardial infarction; PY: patient-years; CI: confidence interval

The Kaplan-Meier-based cumulative event probability is presented in Figure 3 for time to first occurrence of the primary MACE composite endpoint by treatment arm.

Figure 3: Estimated Cumulative Incidence of First MACE

Exacerbations

Trial G also evaluated the effect of TUDORZA PRESSAIR 400 mcg BID on COPD exacerbations. The primary efficacy endpoint was the rate of moderate to severe exacerbations during the first year of treatment, defined as worsening of COPD symptoms (dyspnea, cough, sputum) for at least 2 consecutive days that required treatment with antibiotics and/or systemic corticosteroids or resulted in hospitalization or led to death. In total, 54.3% of patients in Trial G completed the first year of treatment, with 9.8% patients treated less than 12 months due to study closure. TUDORZA PRESSAIR demonstrated a statistically significant reduction in the rate of on-study moderate to severe COPD exacerbations during the first year by 17% compared to placebo (rate ratio [RR] 0.83; 95% CI 0.73 to 0.94; p=0.003). TUDORZA PRESSAIR also demonstrated a statistically significant reduction in the rate of on-study hospitalizations due to COPD exacerbation during the first year by 28% compared with placebo (RR 0.72; 95% CI 0.55 to 0.95; p=0.02).

Figure 4: Time to first moderate or severe COPD exacerbation (days), on-study analysis, Kaplan-Meier plot (Full Analysis Set)

p-value for comparing Aclidinium 400 mcg versus Placebo is based on the Log-rank test stratified by baseline COPD severity and smoking status is p = 0.004.

The Kaplan-Meier curves indicate that the time to first on-study moderate or severe COPD exacerbation was delayed in the aclidinium 400 mcg group compared to the placebo group (see Figure 4). Patients in the aclidinium bromide 400 mcg group had a 15% relative reduction of the risk of an exacerbation (HR 0.85; 95% CI [0.77, 0.95], p=0.004).

16 HOW SUPPLIED/STORAGE AND HANDLING

TUDORZA® PRESSAIR® (aclidinium bromide inhalation powder) 400 mcg is supplied in a sealed bag and is available in 60 metered doses (NDC 0310-0800-60) and 30 metered doses (NDC 0310-0800-39).

The active ingredient is administered using a multi-dose dry powder inhaler, PRESSAIR®, which delivers 60 doses or 30 doses of aclidinium bromide powder for oral inhalation. The PRESSAIR inhaler is a white and green colored device and is comprised of an assembled plastic dosing mechanism with a dose indicator, a drug-product storage unit containing the drug-product formulation, and a mouthpiece covered by a green protective cap.

Store TUDORZA PRESSAIR in a dry place at 25°C (77°F); excursions permitted to 15-30°C (59-86°F) [see USP Controlled Room Temperature]. Do not store the inhaler on a vibrating surface.

The PRESSAIR inhaler should be stored inside the sealed bag and only be opened immediately before use. Throw away the bag.

Throw away (dispose of) the PRESSAIR inhaler after the marking “0” with a red background shows in the middle of the dose indicator, when the device is empty and locks out, or 45 days after the date you opened the sealed bag that the inhaler comes in, whichever comes first.

Keep out of reach of children.

17 PATIENT COUNSELING INFORMATION

See FDA-approved Patient Labeling (Patient Information and Instructions for Use)

- Acute Bronchospasm
  Instruct patients that TUDORZA PRESSAIR is a twice daily maintenance bronchodilator and should not be used for immediate relief of breathing problems (i.e., as a rescue medication) [see Warnings and Precautions (5.1)].
- Paradoxical Bronchospasm
  Inform patients that TUDORZA PRESSAIR can cause paradoxical bronchospasm. Advise patients that if paradoxical bronchospasm occurs, patients should discontinue TUDORZA PRESSAIR [see Warnings and Precautions (5.2)].
- Visual Effects
  Eye pain or discomfort, blurred vision, visual halos, or colored images in association with red eyes from conjunctival congestion and corneal edema may be signs of acute narrow-angle glaucoma. Inform patients to consult a physician immediately should any of these signs and symptoms develop. Advise patients that miotic eyedrops alone are not considered to be effective treatment [see Warnings and Precautions (5.3)].
Inform patients that care must be taken not to allow the powder to enter into the eyes as this may cause blurring of vision and pupil dilation.
- Urinary Retention
  Difficulty passing urine and dysuria may be symptoms of new or worsening prostatic hyperplasia or bladder outlet obstruction. Patients should be instructed to consult a physician immediately should any of these signs or symptoms develop [see Warnings and Precautions (5.4)].
- Immediate Hypersensitivity Reactions
  Inform patients that anaphylaxis, angioedema (including swelling of the lips, tongue, or throat), urticaria, rash, bronchospasm, or itching, may occur after administration of TUDORZA PRESSAIR. Advise patient to immediately discontinue treatment and consult a physician should any of these signs or symptoms develop [see Contraindications (4) and Warnings and Precautions (5.5)].
- Instructions for Administering TUDORZA PRESSAIR
  It is important for patients to understand how to correctly use TUDORZA PRESSAIR.

Inform patients that if they miss a dose, they should take their next dose at the usual time; they should not take 2 doses at one time.

Manufactured for: Covis Pharma,

Zug, 6300 Switzerland

Under license of ALMIRALL, S.A.

TUDORZA® and the logo are registered trademarks of Almirall, S.A., used under license by Covis Pharma.

PRESSAIR® is a registered trademark of the AstraZeneca group of companies, used under license by Covis Pharma.

© 2022 Covis Pharma

Patient Information

TUDORZA® PRESSAIR® (TU-door-za PRESS-air)

(aclidinium bromide inhalation powder)

Important: For oral inhalation only. Do not get TUDORZA PRESSAIR in your eyes.

What is TUDORZA PRESSAIR?

- TUDORZA PRESSAIR is a prescription medicine to treat chronic obstructive pulmonary disease (COPD). COPD is a long-term (chronic) lung disease that includes chronic bronchitis, emphysema, or both.
- TUDORZA PRESSAIR is an anticholinergic medicine. Anticholinergic medicines help the muscles around the airways in your lungs stay relaxed to prevent symptoms such as wheezing, cough, chest tightness, and shortness of breath.
- TUDORZA PRESSAIR is not a rescue medicine and should not be used for treating sudden breathing problems. Your doctor should give you other medicine to use for sudden breathing problems.

It is not known if TUDORZA PRESSAIR is safe and effective in children.

Who should not use TUDORZA PRESSAIR?

Do not use TUDORZA PRESSAIR if you:

- have a severe allergy to milk proteins. Ask your doctor if you are not sure.
- are allergic to aclidinium bromide or any of the ingredients in TUDORZA PRESSAIR. See “What are the ingredients in TUDORZA PRESSAIR?” below for a complete list of ingredients.

What should I tell my doctor before using TUDORZA PRESSAIR?

Before you use TUDORZA PRESSAIR, tell your doctor about all your medical conditions, including if you:

- have eye problems, especially glaucoma. TUDORZA PRESSAIR may make your glaucoma worse.
- have prostate or bladder problems, or problems passing urine. TUDORZA PRESSAIR may make these problems worse.
- are pregnant or plan to become pregnant. It is not known if TUDORZA PRESSAIR can harm your unborn baby.
- are breast-feeding or plan to breast-feed. TUDORZA PRESSAIR may pass into your breast milk. You and your doctor should decide if you will take TUDORZA PRESSAIR.

Tell your doctor about all the medicines you take, including prescription and over-the-counter medicines and eyedrops, vitamins, and herbal supplements.

TUDORZA PRESSAIR and certain other medicines may interact with each other causing serious side effects. Especially tell your doctor if you take:

- other anticholinergic medicines (including tiotropium, ipratropium, umeclidinium, glycopyrrolate).
- atropine.

Know the medicines you take. Keep a list of them to show your doctor and pharmacist each time you get a new medicine.

How should I use TUDORZA PRESSAIR?

- See the “Instructions for Use” for information on how to use TUDORZA PRESSAIR at the end of this Patient Information.
- Use TUDORZA PRESSAIR exactly as prescribed. Do not use TUDORZA PRESSAIR more often than prescribed or take more medicine than prescribed for you.
- The usual dose of TUDORZA PRESSAIR is 1 oral inhalation 2 times a day. Each dose should be about 12 hours apart.
- If you miss a dose of TUDORZA PRESSAIR, skip the missed dose. Take your next dose at your usual time. Do not take 2 doses at one time.
- Do not use other medicines that contain an anticholinergic for any reason. Ask your doctor or pharmacist if any of your other medicines are anticholinergic medicines.
- TUDORZA PRESSAIR does not relieve sudden symptoms of COPD and you should not use extra doses of TUDORZA PRESSAIR to relieve these sudden symptoms. Always have a rescue inhaler medicine with you to treat sudden symptoms. If you do not have a rescue inhaler medicine, call your doctor to have one prescribed for you.
- Call your doctor or get emergency medical care right away if:
  - your breathing problems worsen with TUDORZA PRESSAIR
  - you need to use your rescue inhaler medicine more often than usual
  - your rescue inhaler medicine does not work as well for you at relieving symptoms

What are the possible side effects of TUDORZA PRESSAIR?

TUDORZA PRESSAIR can cause serious side effects including:

- sudden breathing problems immediately after use of TUDORZA PRESSAIR. If you have sudden breathing problems immediately after inhaling TUDORZA PRESSAIR, stop using TUDORZA PRESSAIR and call your doctor right away or go to the nearest hospital emergency room.
- new or worsened increased pressure in your eyes (acute narrow-angle glaucoma). Acute narrow-angle glaucoma can lead to permanent loss of vision if not treated. Symptoms of acute narrow-angle glaucoma may include:

- eye pain or discomfort
- nausea or vomiting

- seeing halos or bright colors around lights

- blurred vision
- red eyes

Using only eyedrops that are used to treat glaucoma is not effective in treating acute narrow-angle glaucoma that can happen with TUDORZA PRESSAIR. If you have any of these symptoms, stop using TUDORZA PRESSAIR and call your doctor right away.
1. new or worsened urinary retention. Urinary retention can be caused by blockage in your bladder or, if you are a male, a larger than normal prostate. Symptoms of urinary retention may include:

- difficulty urinating
- painful urination

- urinating frequently

- urination in a weak stream or drips

If you have any of these symptoms of urinary retention, stop using TUDORZA PRESSAIR and call your doctor right away.
1. serious allergic reactions. Symptoms of a serious allergic reaction may include:

- swelling of the face, lips, tongue, or throat

- hives
- rash

- breathing problems
- itching

If you have any of these symptoms, stop using TUDORZA PRESSAIR and call your doctor or go to the nearest hospital emergency room right away.

The most common side effects of TUDORZA PRESSAIR include:

- headache

- common cold symptoms

- cough

Tell your doctor if you get any side effect that bothers you or does not go away.

These are not all the possible side effects of TUDORZA PRESSAIR. Ask your doctor or pharmacist for more information.

Call your doctor for medical advice about side effects. You may report side effects to FDA at 1-800-FDA-1088.

How should I store TUDORZA PRESSAIR?

- Store TUDORZA PRESSAIR at room temperature between 68°F to 77°F (20°C to 25°C) in the sealed bag that it comes in until you are ready to use TUDORZA PRESSAIR. Do not open the sealed bag until you are ready to use a dose of TUDORZA PRESSAIR. Throw away the bag.
- Keep TUDORZA PRESSAIR in a dry place.
- Do not store the inhaler on a vibrating surface.
- Throw away (dispose of) your TUDORZA PRESSAIR inhaler and use a new one:
  - when the marking “0” with a red background shows in the middle of the dose indicator, or
  - if your inhaler is empty and locks out, or
  - 45 days after the date you opened the sealed bag that the inhaler comes in,
    whichever comes first.

Keep TUDORZA PRESSAIR and all medicines out of the reach of children.

General information about the safe and effective use of TUDORZA PRESSAIR.

Medicines are sometimes prescribed for purposes other than those listed in a Patient Information leaflet. Do not use TUDORZA PRESSAIR for a condition for which it was not prescribed. Do not give TUDORZA PRESSAIR to other people even if they have the same symptoms that you have. It may harm them.

You can ask your doctor or pharmacist for information about TUDORZA PRESSAIR that is written for health professionals.

What are the ingredients in TUDORZA PRESSAIR?

Active ingredient: aclidinium bromide

Inactive ingredient: lactose monohydrate

For more information, go to www.tudorza.com, or call 1-800-411-2510.

This Patient Information has been approved by the U.S. Food and Drug Administration. Revised: August 2022

Instructions for Use

TUDORZA® PRESSAIR® (TU-door-za PRESS-air)

(aclidinium bromide inhalation powder)

For oral inhalation only

This Instructions for Use contains information on how to use your TUDORZA PRESSAIR inhaler. It is important that you read this information as the TUDORZA PRESSAIR inhaler may work differently from inhalers you have used before.

Read this Instructions for Use before you start using TUDORZA PRESSAIR and each time you get a refill. There may be new information. This information does not take the place of talking to your doctor about your medical condition or your treatment.

If you have any questions about how to use your inhaler, ask your doctor, pharmacist, or nurse for help.

The Instructions for Use is divided into the following sections:

  - Getting started
  - Before use
  - Step 1: Prepare your dose
  - Step 2: Inhale your medicine
  - Additional information
  - Questions and Answers about your TUDORZA PRESSAIR Inhaler

Getting Started

Become familiar with the parts of TUDORZA PRESSAIR inhaler (Figure A).

Before use:

1. Right before first use, open the sealed bag at the arrow marking and remove the inhaler. Throw away the bag.
2. Write the date that you open the sealed bag on the label of the inhaler.
3. Do not press the green button until you are ready to take a dose.
4. Remove the protective cap by lightly squeezing the arrows marked on each side of the protective cap and pulling straight off (Figure B).

Step 1: Prepare your dose

1.1 Look in the opening of the mouthpiece and make sure nothing is blocking it (Figure C).

1.2 Look at the control window. The control window should be red (Figure C).

1.3 Hold the inhaler horizontally with the mouthpiece facing you and the green button on top (Figure D).

1.4 Press the green button all the way down to load your dose (Figure E).

When you press the green button all the way down, the control window changes from red to green.

Make sure the green button is on top. Do not tilt the inhaler.

1.5 Release the green button (Figure F).

Make sure you release the green button, so the inhaler can work correctly.

Stop and Check:

1.6 Make sure the control window is now green (Figure G).
This means your medicine is ready to be inhaled.
Go to “Step 2: Inhale your medicine”.

What to do if the control window is still red after pressing the button (Figure H).

The dose is not prepared. Go back to “Step 1: Prepare your dose” and repeat steps 1.1 to 1.6.

Step 2: Inhale your medicine

Read steps 2.1 to 2.7 fully before use. Do not tilt the inhaler.

2.1 Hold the inhaler away from your mouth, and breathe out completely. Never breathe out into the inhaler (Figure I).

2.2 Hold your head upright, put the mouthpiece between your lips, and close your lips tightly around the mouthpiece (Figure J).

Do not hold the green button down while inhaling

2.3 Take a strong, deep breath through your mouth. Keep breathing in for as long as possible.

A “click” will let you know that you are inhaling correctly. Keep breathing in as long as possible after you hear the “click”. Some people may not hear the “click”. Use the control window to make sure you have inhaled correctly.

2.4 Take the inhaler out of your mouth.

2.5 Hold your breath for as long as possible.

2.6 Slowly breathe out, away from the inhaler.

Some people may have a grainy sensation in their mouth, or a slightly sweet or bitter taste. Do not take an extra-dose if you do not taste or feel anything after inhaling.

Stop and Check:

2.7 Make sure the control window is now red (Figure K). This means you have inhaled your medicine correctly.

What to do if the control window is still green after inhalation (Figure L).

This means you have not inhaled your medicine correctly. Go back to “Step 2: Inhale your medicine” and repeat steps 2.1 to 2.7.

If the control window still does not change to red, you may have forgotten to release the green button before inhaling, or you may not have inhaled strongly enough. If this happens, try again. Make sure you have released the green button, and you have breathed out completely. Then take a strong, deep breath through the mouthpiece.

Contact your doctor if the control window is still green after repeated attempts.

Push the protective cap back onto the mouthpiece after each use (Figure M) to prevent contamination of the inhaler with dust or other materials. You should throw away (dispose of) your inhaler if you lose the cap.

For more information about TUDORZA PRESSAIR and a video demonstration on how to use TUDORZA PRESSAIR, go to www.tudorza.com.

Additional information

What should I do if I accidentally prepare a dose?

Store your inhaler with the protective cap in place until it is time to inhale your medicine, then remove the cap and start at Step 1.6.

How does the dose indicator work?

- The dose indicator shows the total number of doses left in the inhaler (Figure N).
- On first use, every inhaler contains at least 60 doses.

Each time you load a dose by pressing the green button, the dose indicator moves by a small amount towards the next number (50, 40, 30, 20, 10, or 0).

When should I get a new inhaler?

You should throw away (dispose of) your inhaler if it appears to be damaged or if you lose the protective cap.

When a red band appears in the dose indicator, this means you are close to your last dose (Figure N).

You should throw away (dispose of) the inhaler and use a new one:

- when the marking “0” with a red background shows in the middle of the dose indicator (Figure O), or
- if your inhaler is empty and locks out (Figure P), or
- 45 days after the date you opened the sealed bag that the inhaler comes in,
- whichever comes first.

How do I know that my inhaler is empty?

- When the green button will not return to its full upper position and is locked in a middle position (Figure P). Even though the green button is locked, your last dose may still be inhaled. After that, the inhaler cannot be used again and you should start using a new inhaler.

How should I clean the inhaler?

Never use water to clean the inhaler, as this may damage your medicine.

If you want to clean your inhaler, wipe the outside of the mouthpiece with a dry tissue or paper towel.

How should I store TUDORZA PRESSAIR?

- Store TUDORZA PRESSAIR at room temperature between 68°F to 77°F (20°C to 25°C) in the sealed bag that it comes in until you are ready to use TUDORZA PRESSAIR. Do not open the sealed bag until you are ready to use a dose of TUDORZA PRESSAIR.
- Keep TUDORZA PRESSAIR in a dry place.
- Do not store the inhaler on a vibrating surface.

Keep TUDORZA PRESSAIR and all medicines out of the reach of children.

Questions and Answers about your TUDORZA PRESSAIR Inhaler

Question

Answer

Do I need to take extra steps to prepare the inhaler before first use?

TUDORZA PRESSAIR comes preloaded with medicine and is ready to use. Remove the inhaler from the sealed bag and follow the step-by-step Instructions for Use.

How do I know if the TUDORZA PRESSAIR inhaler is ready to use before taking each dose?

The TUDORZA PRESSAIR inhaler is ready to use when the control window on the front of the inhaler is green (Figure G).

- If the control window is red (see Step 1.6), press and release the green button completely. This will change the color of the control window from red to green, indicating the medicine is ready to inhale.

What if the TUDORZA PRESSAIR inhaler window does not change from red to green?

The dose is not prepared. Go back to “Step 1: Prepare your dose” and repeat steps 1.1 to 1.6.

- If the green button is locked, you have used all the medicine in your inhaler and should get a new TUDORZA PRESSAIR inhaler (Figure P).

How do I know that I used TUDORZA PRESSAIR correctly?

The TUDORZA PRESSAIR inhaler has a helpful feature to let you know that you have inhaled your medicine correctly.

- Look at the control window to see if it has turned to red after you have inhaled fully through the mouthpiece. If the control window is red you have inhaled your full dose of medicine correctly (see Step 2.7).

What if the TUDORZA PRESSAIR inhaler control window does not change color from green back to red after I inhale?

This means you may not have inhaled the medicine strongly enough. Go back to “Step 2: Inhale your medicine” and repeat steps 2.1 to 2.7.

- Did you breathe out completely before inhaling?
- Did you let go of the green button before inhaling?
- Did you form a tight seal with your lips around the mouthpiece?
- Did you breathe in strongly and deeply?
- Did you keep breathing in after you heard the “click”?

What if I do not see the dose indicator move after I inhaled?

Each time you load a dose by pressing the green button, the dose indicator moves by a small amount towards the next number from 60 to 0: 60, 50, 40, 30, 20, 10, 0 (see Figure N). If you see the control window change from green to red, you have successfully inhaled the full dose.

Can the TUDORZA PRESSAIR inhaler release too much medicine or lose doses of medicine from the inhaler?

No. The TUDORZA PRESSAIR inhaler only releases 1 dose of medicine with each inhalation. Pressing and releasing the green button more than one time before inhaling does not increase the dose you will receive or cause any medicine to be lost.

This Instructions for Use has been approved by the U.S. Food and Drug Administration.

Manufactured for:

Covis Pharma

Zug, 6300 Switzerland

Under license of ALMIRALL, S.A.

TUDORZA® and the logo are registered trademarks of Almirall, S.A., used under license by Covis Pharma.

PRESSAIR® is a registered trademark of the AstraZeneca group of companies, used under license by Covis Pharma.

Revised: August, 2022

PRINCIPAL DISPLAY PANEL - 60 Metered Doses Carton

Carton - 60 Metered Doses

NDC 70515-002-01

Rx only

Tudorza® Pressair®
(aclidinium bromide inhalation powder)
400 mcg per actuation
For Oral Inhalation

60 Metered Doses

COVIS